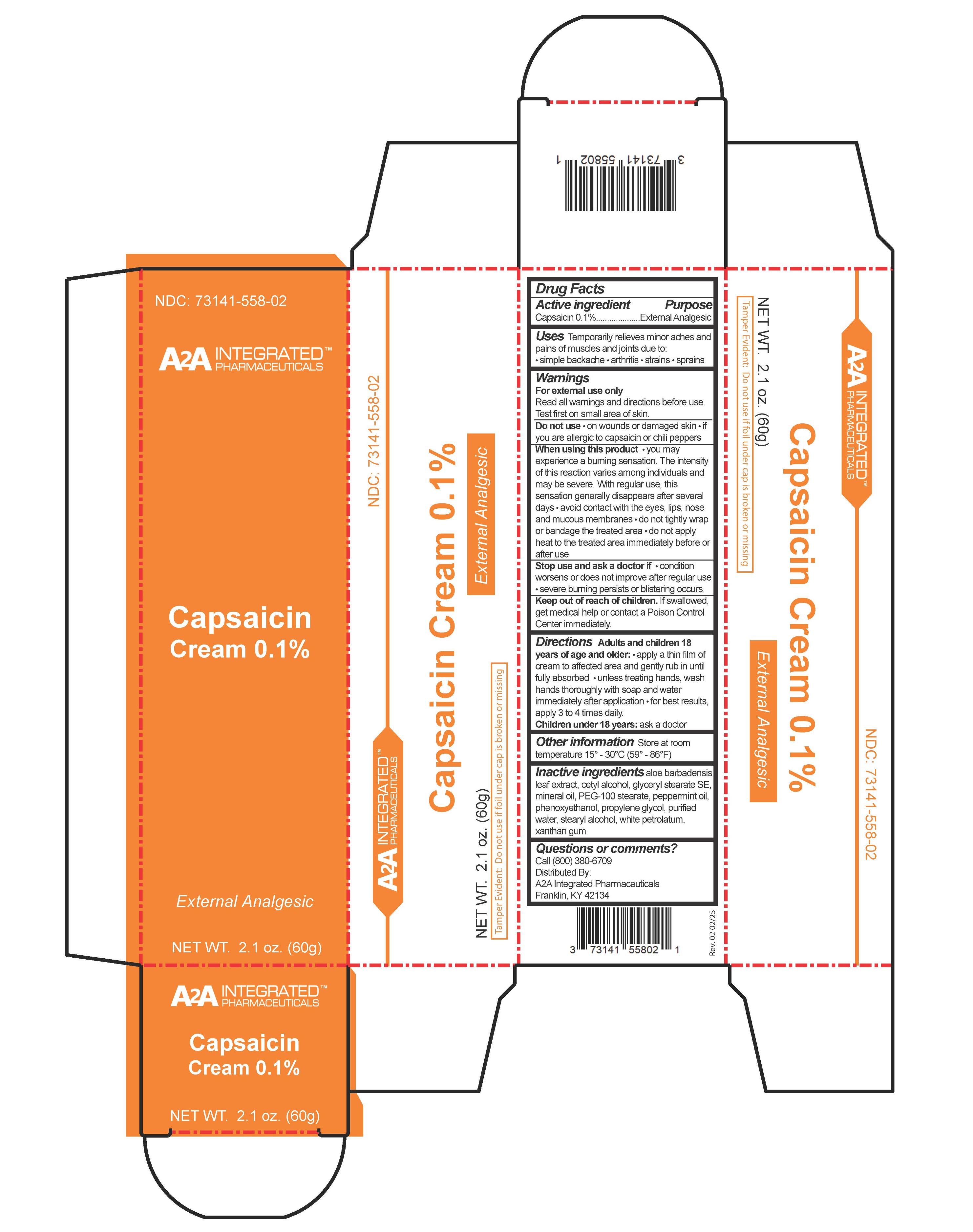 DRUG LABEL: Capsaicin Cream
NDC: 73141-558 | Form: CREAM
Manufacturer: A2A Integrated Pharmaceuticals, LLC
Category: otc | Type: HUMAN OTC DRUG LABEL
Date: 20251130

ACTIVE INGREDIENTS: CAPSAICIN 0.1 g/100 g
INACTIVE INGREDIENTS: WATER; PEG-100 STEARATE; PROPYLENE GLYCOL; CETYL ALCOHOL; PEPPERMINT OIL; PHENOXYETHANOL; ALOE VERA LEAF; MINERAL OIL; XANTHAN GUM; WHITE PETROLATUM; GLYCERYL STEARATE SE; STEARYL ALCOHOL

A2A Capsaicin Cream

ACTIVE INGREDIENT

Capsaicin 0.1%

PURPOSE

External Analgesic

Uses

Temporarily relieves minor aches and pains of muscles and joints due to

simple backache
arthritis
strains
sprains

Warnings

For external use only

Read all warnings and directions before use. Test first on small area of skin.

Do not use:

on wounds or damaged skin
if you are allergic to capsaicin or chili peppers

When using this product:

you may experience a burning sensation. The intensity of this reaction varies among individuals and may be severe. with regular use, this sensation generally disappears after several days
avoid contact with the eyes, lips, nose, and mucous membranes
do not tightly wrap or bandage the treated area
do not apply heat to the treated area immediately before or after use.

Ask Doctor

Stop use and ask a doctor if:

condition worsens or does not improve after regular use
severe burning persists or blistering occurs.

Keep out of Reach of Children

Keep out of reach of children. If swallowed, get medical help or contact a Poison Control Center immediately

DOSAGE AND ADMINISTRATION

Adults and children 18 years of age and older:

apply a thin film of cream to affected area and gently tub in until fully absorbed
unless treating hands, wash hands thoroughly with soap and water immediately after application
for best results apply 3 to 4 times daily.

Children under 18 years: ask a doctor

Other Information: Store at room temperature 15°- 30°C (59° - 86°F)

INACTIVE INGREDIENT

aloe barbadensis leaf extract, cetyl alcohol, glyceryl stearate SE, mineral oil, PEG-100 stearate, peppermint oil, phenoxyethanol, propylene glycol, purified water, stearyl alcohol, white petrolatum, xanthan gum.

Questions or comments?

Call (800) 380-6709

Distributed By:

A2A Integrated Pharmaceuticals

Franklin, KY 42134